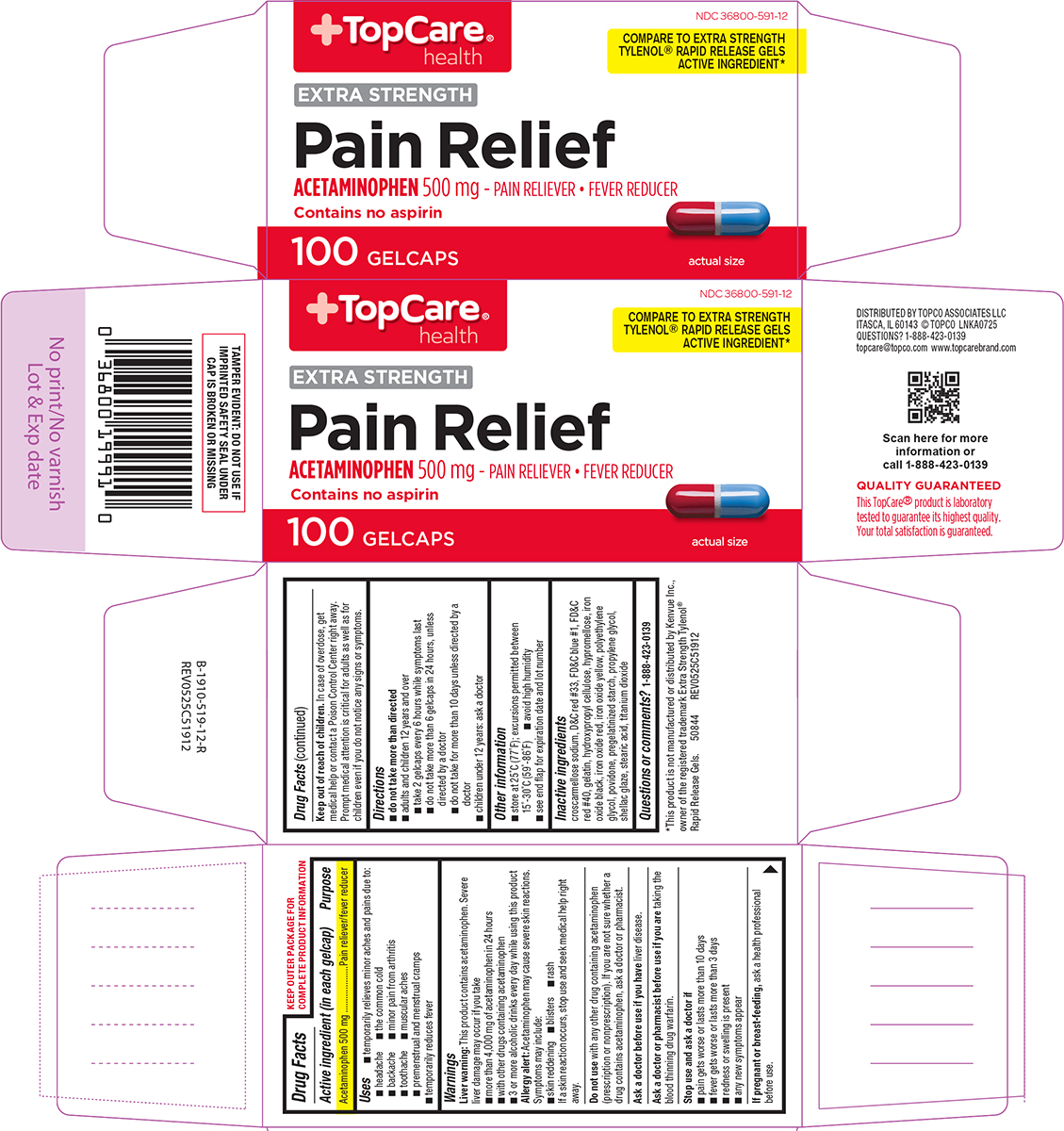 DRUG LABEL: Pain Relief
NDC: 36800-591 | Form: TABLET, COATED
Manufacturer: Topco Associates, LLC
Category: otc | Type: HUMAN OTC DRUG LABEL
Date: 20260210

ACTIVE INGREDIENTS: ACETAMINOPHEN 500 mg/1 1
INACTIVE INGREDIENTS: CROSCARMELLOSE SODIUM; D&C RED NO. 33; FD&C BLUE NO. 1; FD&C RED NO. 40; GELATIN, UNSPECIFIED; HYDROXYPROPYL CELLULOSE, UNSPECIFIED; HYPROMELLOSE, UNSPECIFIED; FERROSOFERRIC OXIDE; FERRIC OXIDE RED; FERRIC OXIDE YELLOW; POLYETHYLENE GLYCOL, UNSPECIFIED; POVIDONE, UNSPECIFIED; STARCH, CORN; PROPYLENE GLYCOL; SHELLAC; STEARIC ACID; TITANIUM DIOXIDE

Topcare 44-519

Active ingredient (in each gelcap)

Acetaminophen 500 mg

Purpose

Pain reliever/fever reducer

Uses

- temporarily relieves minor aches and pains due to:
  - headache
  - the common cold
  - backache
  - minor pain from arthritis
  - toothache
  - muscular aches
  - premenstrual and menstrual cramps
- temporarily reduces fever

Warnings

Liver warning: This product contains acetaminophen. Severe liver damage may occur if you take

- more than 4,000 mg of acetaminophen in 24 hours
- with other drugs containing acetaminophen
- 3 or more alcoholic drinks every day while using this product

Allergy alert: Acetaminophen may cause severe skin reactions. Symptoms may include:

- skin reddening
- blisters
- rash

If a skin reaction occurs, stop use and seek medical help right away.

Do not use

with any other drug containing acetaminophen (prescription or nonprescription). If you are not sure whether a drug contains acetaminophen, ask a doctor or pharmacist.

Ask a doctor before use if you have

liver disease.

Ask a doctor or pharmacist before use if you are

taking the blood thinning drug warfarin.

Stop use and ask a doctor if

- pain gets worse or lasts more than 10 days
- fever gets worse or lasts more than 3 days
- redness or swelling is present
- any new symptoms appear

If pregnant or breast-feeding,

ask a health professional before use.

Keep out of reach of children.

In case of overdose, get medical help or contact a Poison Control Center right away. Prompt medical attention is critical for adults as well as for children even if you do not notice any signs or symptoms.

Directions

- do not take more than directed
- adults and children 12 years and over
  - take 2 gelcaps every 6 hours while symptoms last
  - do not take more than 6 gelcaps in 24 hours, unless directed by a doctor
  - do not take for more than 10 days unless directed by a doctor
- children under 12 years: ask a doctor

Other information

- store at 25°C (77°F); excursions permitted between 15°-30°C (59°-86°F)
- avoid high humidity
- see end flap for expiration date and lot number

Inactive ingredients

croscarmellose sodium, D&C red #33, FD&C blue #1, FD&C red #40, gelatin, hydroxypropyl cellulose, hypromellose, iron oxide black, iron oxide red, iron oxide yellow, polyethylene glycol, povidone, pregelatinized starch, propylene glycol, shellac glaze, stearic acid, titanium dioxide

Questions or comments?

1-888-423-0139

Principal Display Panel

+TopCare®
health

NDC 36800-591-12

COMPARE TO EXTRA STRENGTH
TYLENOL® RAPID RELEASE GELS
ACTIVE INGREDIENT*

EXTRA STRENGTH
Pain Relief
ACETAMINOPHEN 500 mg - PAIN RELIEVER • FEVER REDUCER

actual size

100 GELCAPS

TAMPER EVIDENT: DO NOT USE IF
IMPRINTED SAFETY SEAL UNDER
CAP IS BROKEN OR MISSING

*This product is not manufactured or distributed by Kenvue Inc.,
owner of the registered trademark Extra Strength Tylenol®
Rapid Release Gels. 50844 REV0525C51912

DISTRIBUTED BY TOPCO ASSOCIATES LLC
ITASCA, IL 60143 © TOPCO LNKA0725
QUESTIONS? 1-888-423-0139
topcare@topco.com www.topcarebrand.com

Scan here for more
information or
call 1-888-423-0139

QUALITY GUARANTEED
This TopCare® product is laboratory
tested to guarantee its highest quality.
Your total satisfaction is guaranteed.

TopCare 44-519